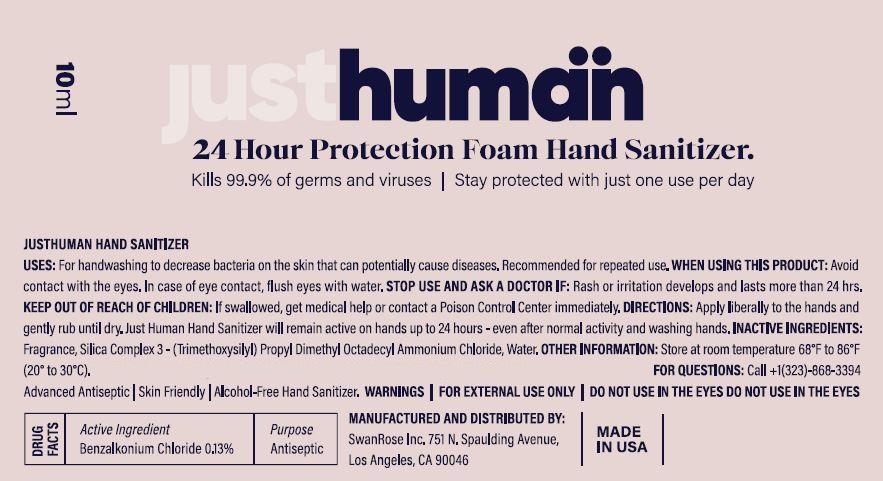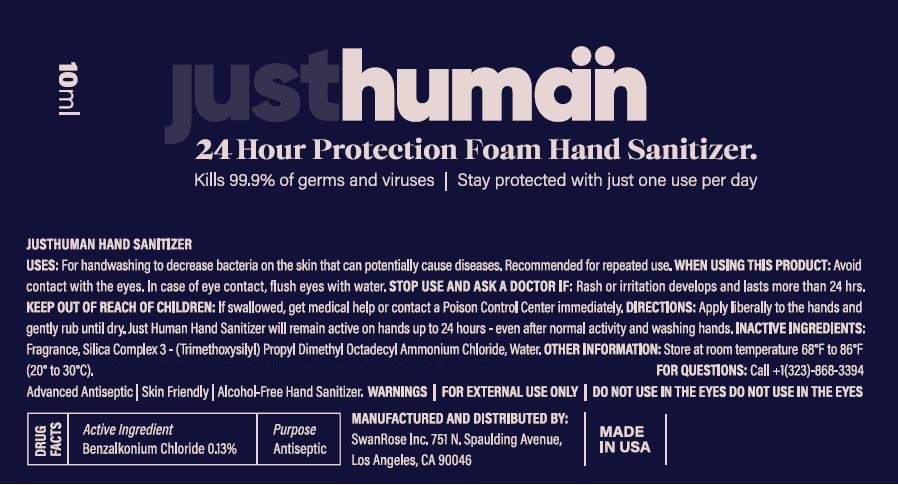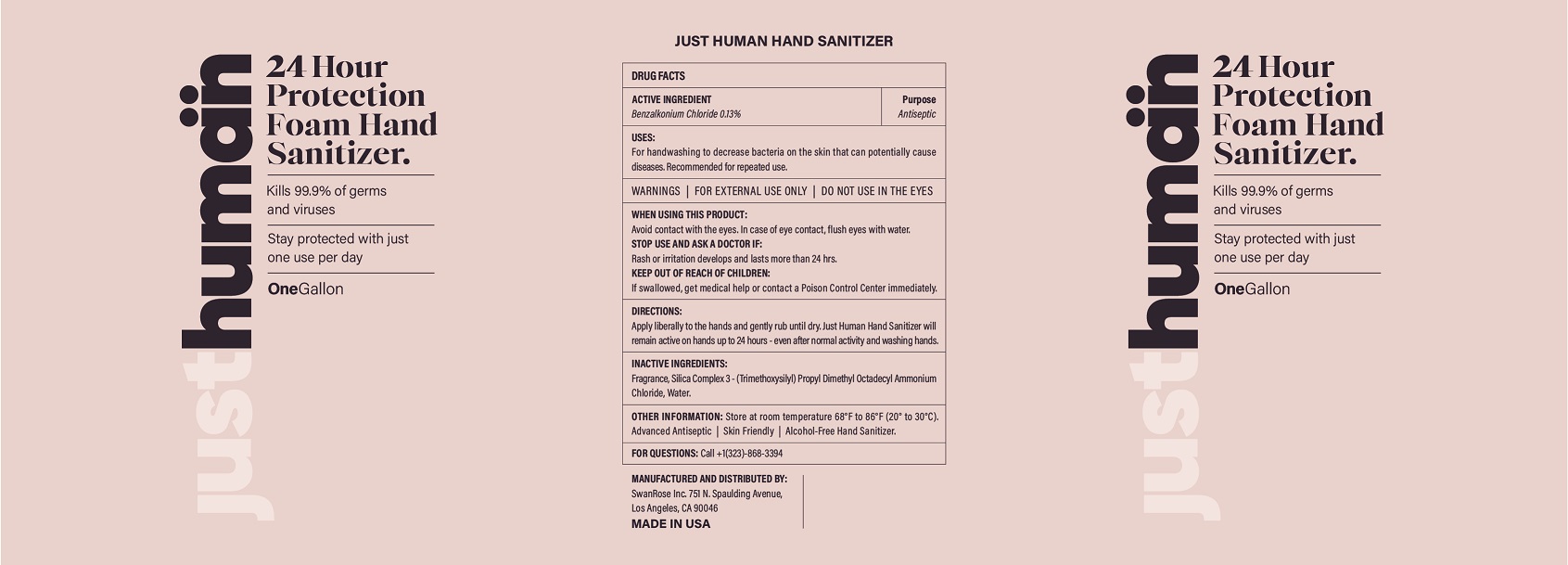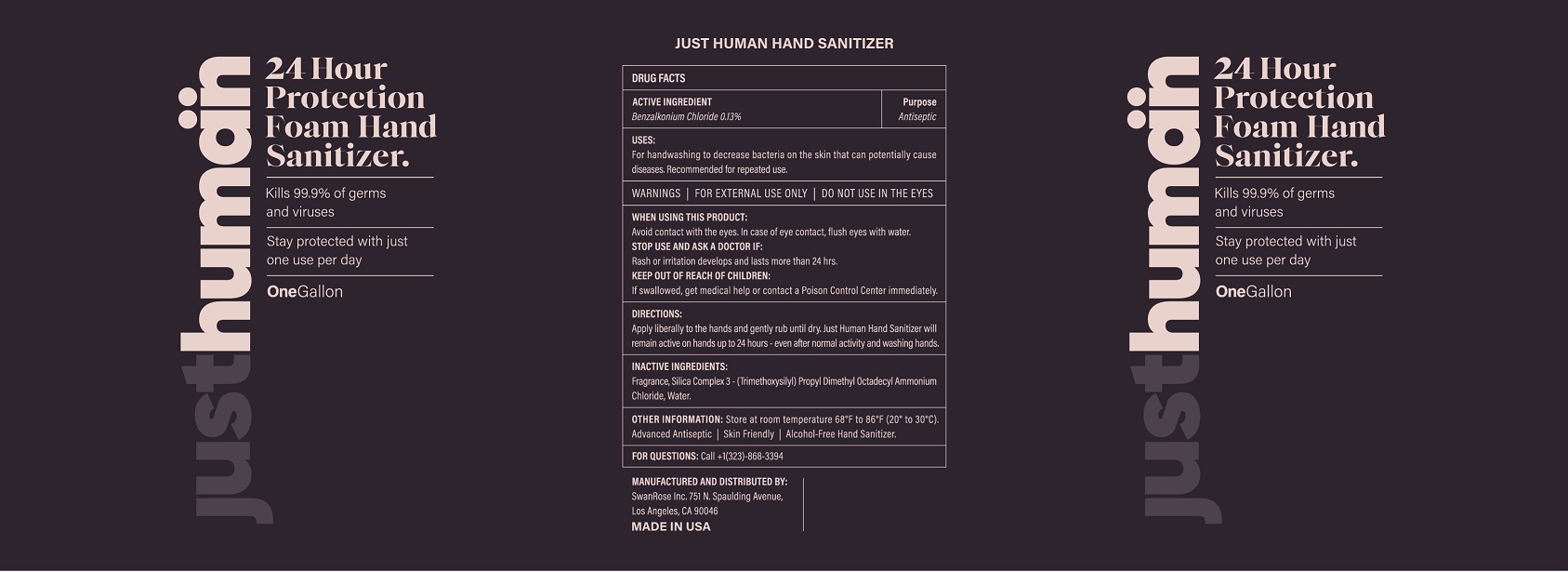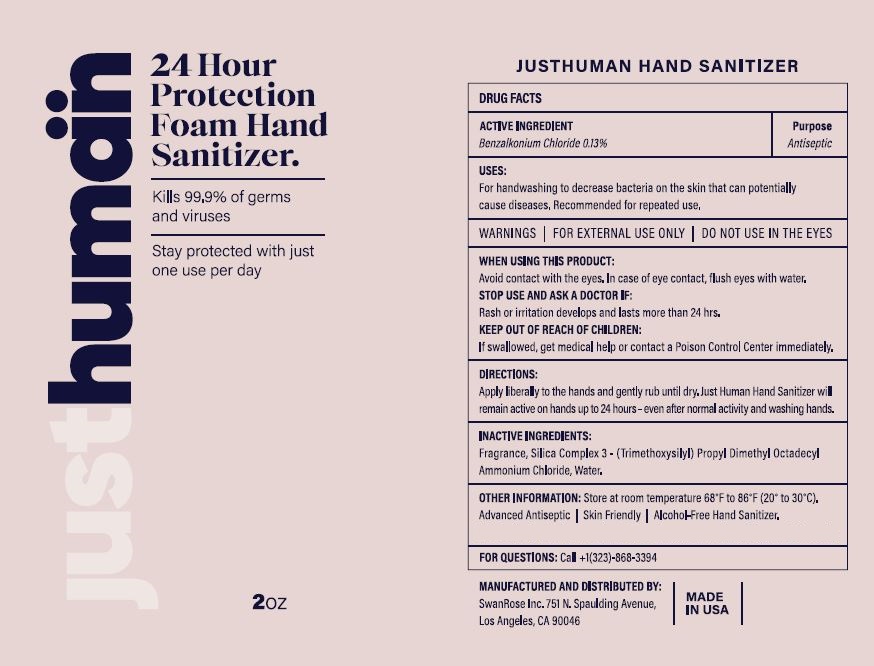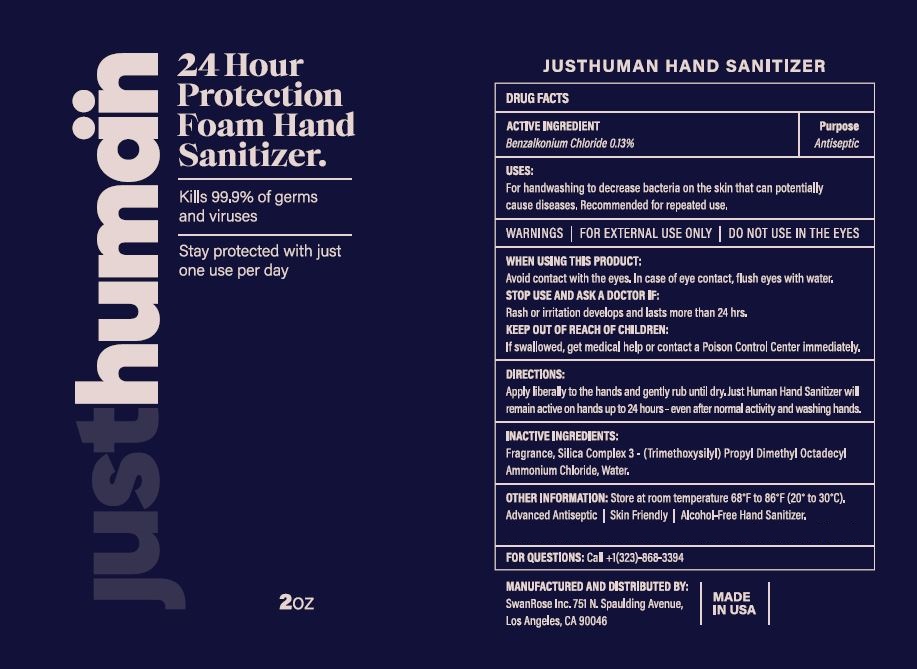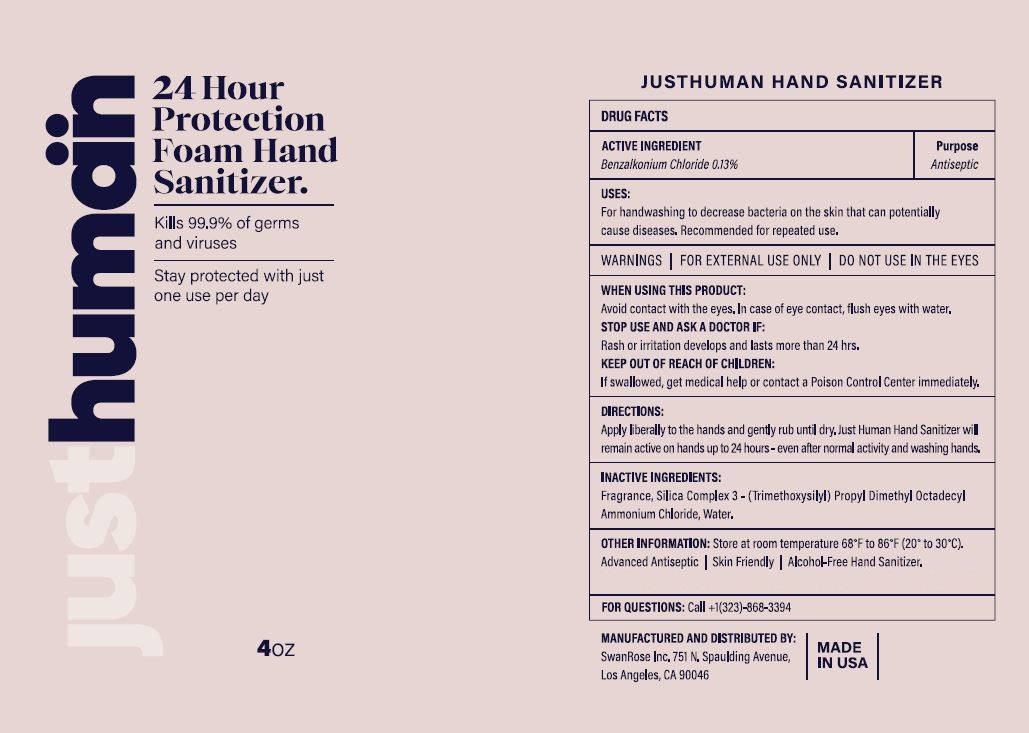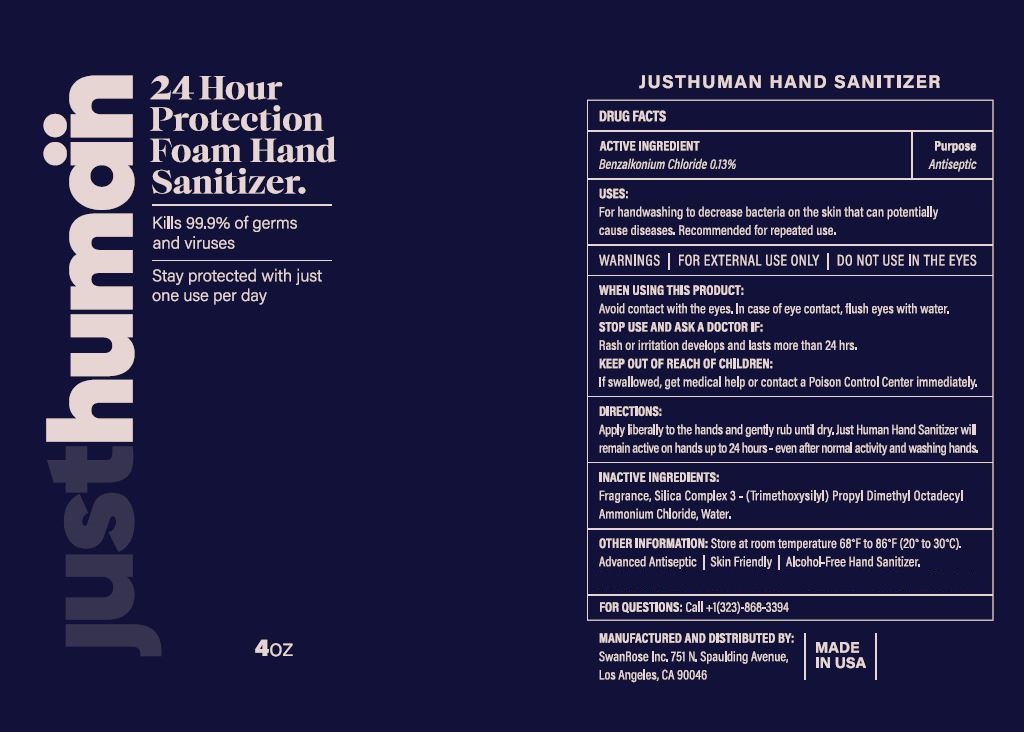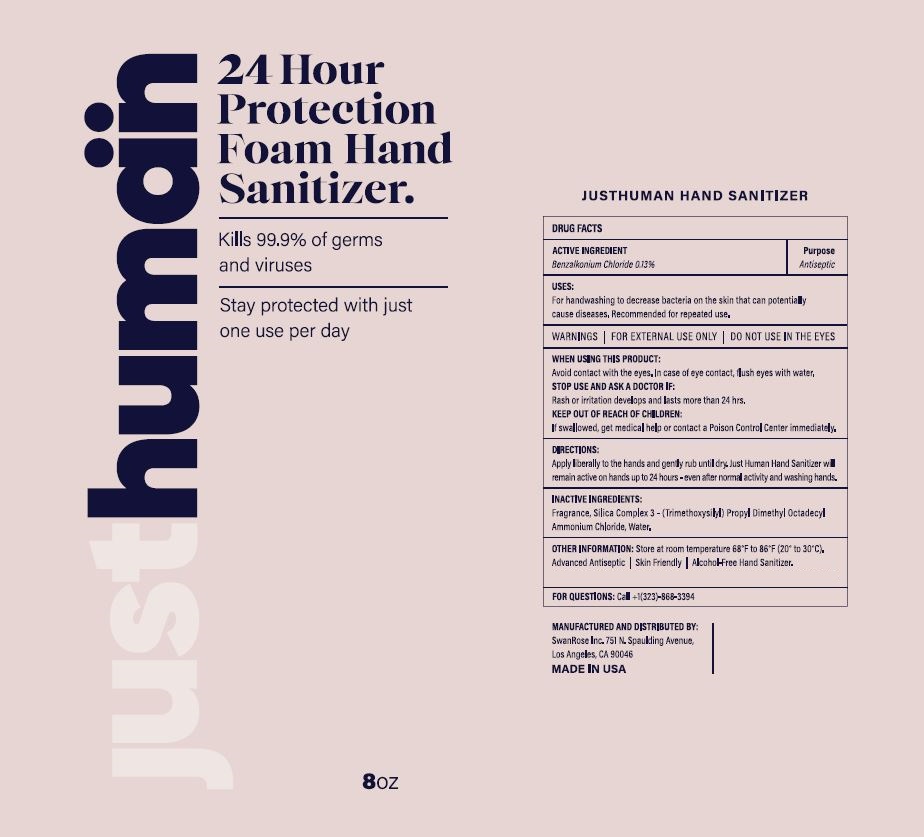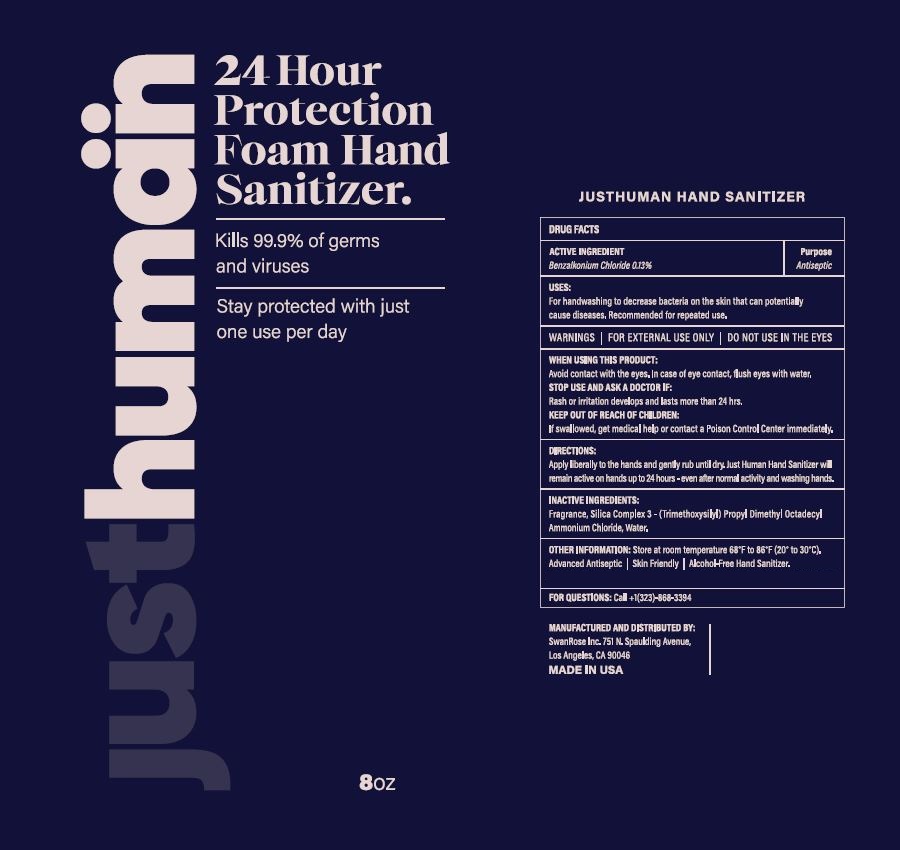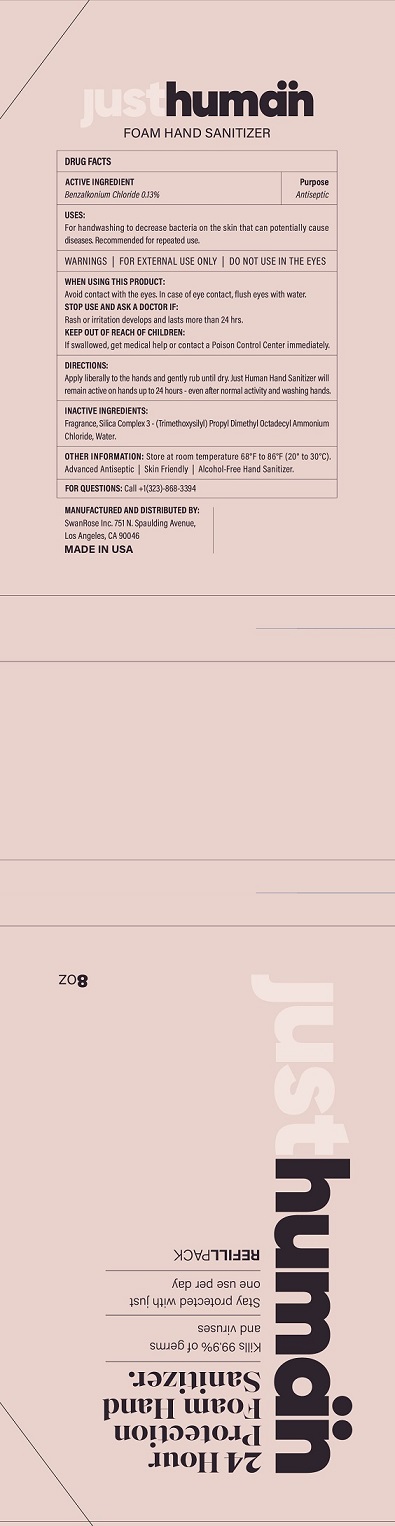 DRUG LABEL: Justhuman 24 Hour Protection Foam Hand Sanitizer
NDC: 78287-250 | Form: SOLUTION
Manufacturer: Swanrose Inc.
Category: otc | Type: HUMAN OTC DRUG LABEL
Date: 20210218

ACTIVE INGREDIENTS: BENZALKONIUM CHLORIDE 0.13 kg/1 kg
INACTIVE INGREDIENTS: DIMETHYLOCTADECYL(3-(TRIMETHOXYSILYL)PROPYL)AMMONIUM CHLORIDE; WATER

ACTIVE INGREDIENT

Benzalkonium Chloride 0.13%............................Antiseptic

Purpose

Antiseptic

USES:

For handwashing to decrease bacteria on the skin that can potentially cause disease.

Recommended for repeated use.

WARNINGS

- FOR EXTERNAL USE ONLY
- DO NOT USE IN THE EYES

WHEN USING THS PRODUCT:

- Avoid contact with the eyes. In case of eye contact, flush eyes with water.

STOP USE AND ASK A DOCTOR IF:

- Rash or irritation develops and lasts more than 24 hrs.

KEEP OUT OF REACH OF CHILDREN:

- If swallowed, get medical help or contact a Poison Control Center immediately.

DIRECTIONS:

- Apply liberally to the hands and gently rub until dry. Just Human Hand Sanitizer will remain active on hands up to 24 hours - even after normal activity and washing hands.

INACTIVE INGREDIENTS:

Fragrance, Silica Complex 3-(Trimethoxysilyl) Propyl Dimethyl Octadecyl Ammonium Chloride, Water

OTHER INFORMATION:

Store at temperature 68°F to 86°F (20° to 30°C)

Advanced Antiseptic \ Skin Freindly \ Alcohol-Free Hand Sanitizer

FOR QUESTIONS:

Call +1(323-868-3394